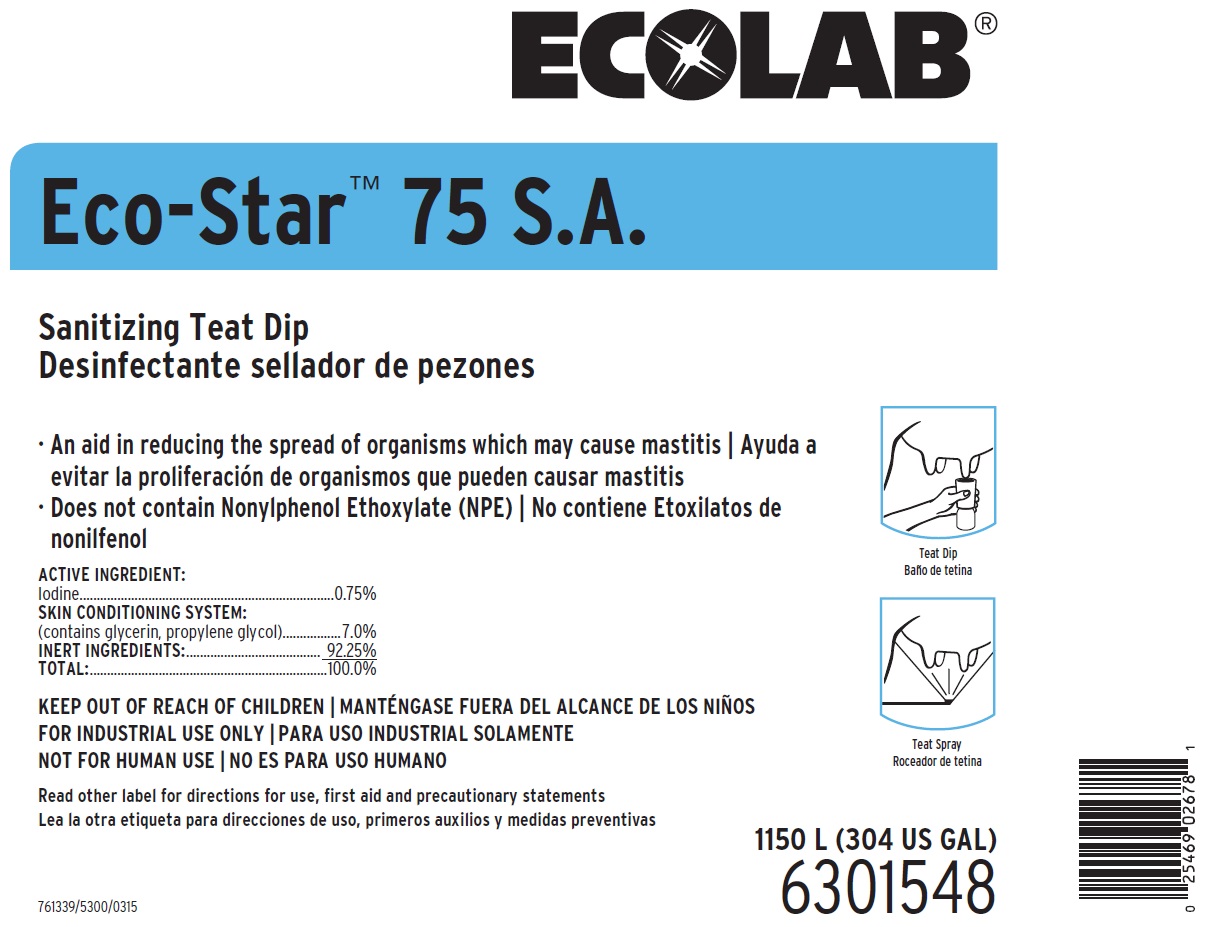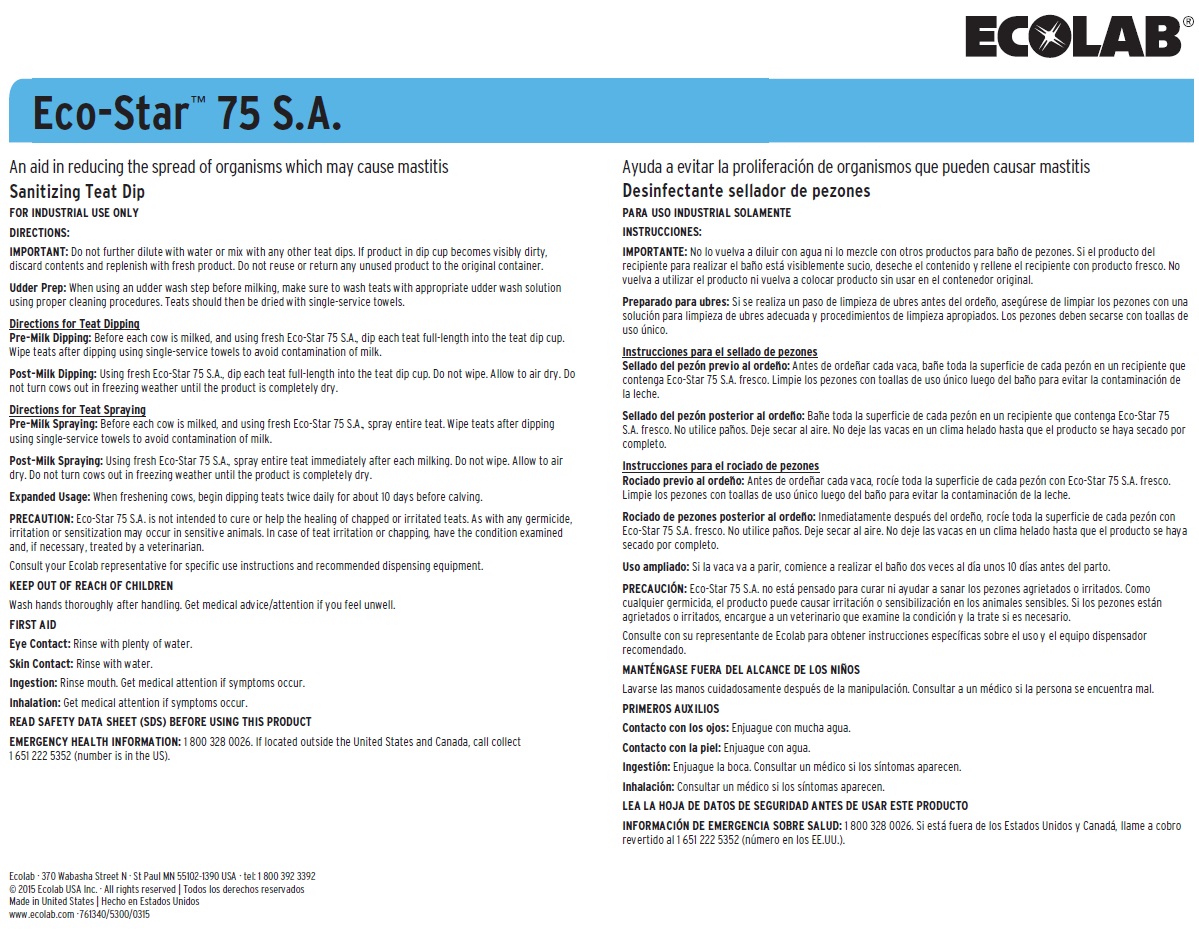 DRUG LABEL: Eco-Star 75 S.A.
NDC: 47593-529 | Form: SOLUTION
Manufacturer: Ecolab Inc.
Category: animal | Type: OTC ANIMAL DRUG LABEL
Date: 20251027

ACTIVE INGREDIENTS: IODINE 7.5 mg/1 mL
INACTIVE INGREDIENTS: WATER; GLYCERIN; PROPYLENE GLYCOL

KEEP OUT OF REACH OF CHILDREN

FOR INDUSTRIAL USE ONLY

NOT FOR HUMAN USE

Read other label for directions for use, first aid and precautionary statements

Wash hands thoroughly after handling. Get medical advice/attention if you feel unwell.

DIRECTIONS:

IMPORTANT: Do not further dilute with water or mix with any other teat dips. If product in dip cup becomes visibly dirty, discard contents and replenish with fresh product. Do not reuse or return any unused product to the original container.

Udder Prep: When using an udder wash step before milking, make sure to wash teats with appropriate udder wash solution using proper cleaning procedures. Teats should then be dried with single-service towels.

Directions for Teat Dipping

Pre-Milk Dipping: Before each cow is milked, and using fresh Eco-Star 75 S.A., dip each teat full-length into the teat dip cup. Wipe teats after dipping using single-service towels to avoid contamination of milk.

Post-Milk Dipping: Using fresh Eco-Star 75 S.A., dip each teat full-length into the teat dip cup. Do not wipe. Allow to air dry. Do not turn cows out in freezing weather until the product is completely dry.

Directions for Teat Spraying

Pre-Milk Spraying: Before each cow is milked, and using fresh Eco-Star 75 S.A., spray entire teat. Wipe teats after dipping using single-service towels to avoid contamination of milk.

Post-Milk Spraying: Using fresh Eco-Star 75 S.A., spray entire teat immediately after each milking. Do not wipe. Allow to air dry. Do not turn cows out in freezing weather until the product is completely dry.

Expanded Usage: When freshening cows, begin dipping teats twice daily for about 10 days before calving.

PRECAUTION: Eco-Star 75 S.A. is not intended to cure or help the healing of chapped or irritated teats. As with any germicide, irritation or sensitization may occur in sensitive animals. In case of teat irritation or chapping, have the condition examined and, if necessary, treated by a veterinarian.

Consult your Ecolab representative for specific use instructions and recommended dispensing equipment.

OTHER SAFETY INFORMATION

FIRST AID

Eye Contact: Rinse with plenty of water.

Skin Contact: Rinse with water.

Ingestion: Rinse mouth. Get medical attention if symptoms occur.

Inhalation: Get medical attention if symptoms occur.

READ SAFETY DATA SHEET (SDS) BEFORE USING THIS PRODUCT

EMERGENCY HEALTH INFORMATION: 1 800 328 0026. If located outside the United States and Canada, call collect 1 651 222 5352 (number is in the US).

Representative label and principal display panel

ECOLAB

Eco-Star™ 75 S.A.

Sanitizing Teat Dip

An aid in reducing the spread of organisms which may cause mastitis

Does not contain Nonylphenol Ethoxylate (NPE)

ACTIVE INGREDIENT:

Iodine..........................................................................0.75%

SKIN CONDITIONING SYSTEM:

(contains glycerin, propylene glycol).................7.0%

INERT INGREDIENTS: ....................................... 92.25%

TOTAL: .....................................................................100.0%

1150 L (304 US GAL)

6301548

Ecolab · 370 Wabasha Street N · St Paul MN 55102-1390 USA · tel: 1 800 392 3392

© 2015 Ecolab USA Inc. · All rights reserved

Made in United States

www.ecolab.com ·761340/5300/0315